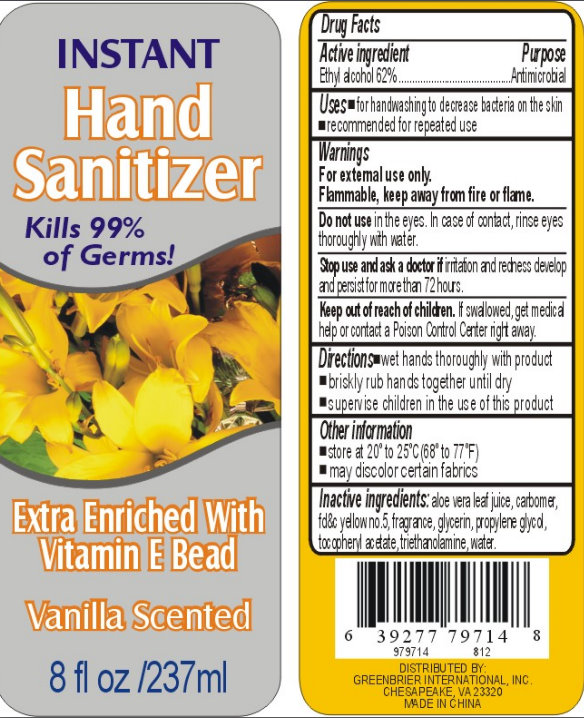 DRUG LABEL: Instant  Hand Sanitizer - Vanilla Scented
NDC: 10586-9102 | Form: LIQUID
Manufacturer: Core Brands, Inc.
Category: otc | Type: HUMAN OTC DRUG LABEL
Date: 20111103

ACTIVE INGREDIENTS: ALCOHOL 62 mL/100 mL
INACTIVE INGREDIENTS: ALOE VERA LEAF; FD&C YELLOW NO. 5; GLYCERIN; PROPYLENE GLYCOL; ALPHA-TOCOPHEROL ACETATE; WATER

Instant Hand Sanitizer Extra Enriched With Vitamin E Bead Vanilla Scented

Active ingredient

Ethyl Alcohol 62%

Purpose

Antimicrobial

Uses

- for handwashing to decrease bacteria on the skin
- recommended for repeated use

Warnings

For external use only.

Flammable, keep away from fire or flame.

Do not use

in the eyes. In case of contact, rinse eyes thoroughly with water.

Stop use and ask a doctor if

irritation and redness develop and persist for more than 72 hours.

Keep out of reach of children.

If swallowed, get medical help or contact a Poison Control Center right away.

Directions

- wet hands thoroughly with product
- briskly rub hands together until dry
- supervise children in the use of this product

Other information

- store at 20 degrees to 25 degrees C (68 degrees to 77 degrees F)
- may discolor certain fabrics

Inactive ingredients:

aloe vera leaf juice, carbomer, fd c yellow no.5, fragrance, glycerin, propylene glycol, tocpheryl acetate, triethanolamine, water.